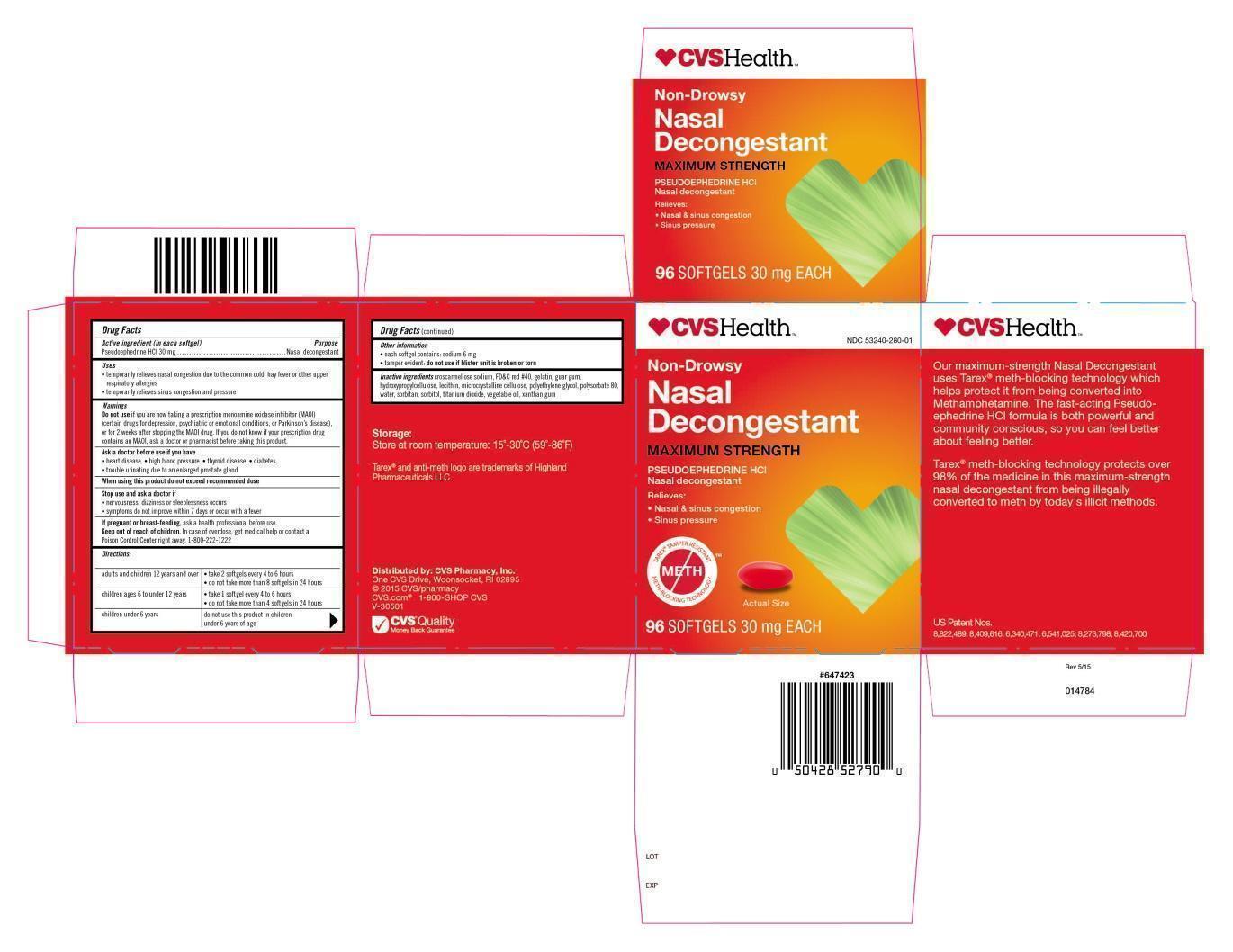 DRUG LABEL: CVS Health Non-Drowsy Nasal Decongestant
NDC: 53240-280 | Form: PILL
Manufacturer: Westport Pharmaceuticals
Category: otc | Type: HUMAN OTC DRUG LABEL
Date: 20151007

ACTIVE INGREDIENTS: PSEUDOEPHEDRINE HYDROCHLORIDE 30 mg/1 1
INACTIVE INGREDIENTS: CROSCARMELLOSE SODIUM; GUAR GUM; HYDROXYPROPYL CELLULOSE, LOW SUBSTITUTED; LECITHIN, SOYBEAN; CELLULOSE, MICROCRYSTALLINE; POLYETHYLENE GLYCOL 3350; SORBITAN; HYDROGENATED PALM KERNEL OIL; XANTHAN GUM; FD&C RED NO. 40; GELATIN; POLYSORBATE 80; WATER; SORBITOL; TITANIUM DIOXIDE

Active Ingredients (in each pill)

Pseudoephedrine HCl 30 mg

Purpose

Nasal Decongestant

Keep out of reach of children. In case of overdose, get medical help or contact a

Poison Control Center right away. (1-800-222-1222)

Uses

- temporarily relieves nasal congestion due to the common cold, hay fever, or other upper respiratory allergies
- temporarily relieves sinus congestion and pressure

Warnings

Do not use if you are now taking a prescription monoamine oxidase inhibitor (MAOI)

(certain drugs for depression, psychiatric or emotional conditions, or Parkinson’s disease),

or for 2 weeks after stopping the MAOI drug. If you do not know if your prescription drug

contains an MAOI, ask a doctor or pharmacist before taking this product.

Ask a doctor before use if you have

• heart disease • high blood pressure • thyroid disease • diabetes

• trouble urinating due to an enlarged prostate gland

When using this product do not exceed recommended dose

Stop and ask a doctor if

- nervousness, dizziness or sleeplessness occur
- symptoms do not improve within 7 days or occur with a fever

If pregnant or breast-feeding, ask a health professional before use.

DOSAGE AND ADMINISTRATION

Directions: remove pill from sealed, plastic packaging before ingesting

swallow whole – do not crush, chew or dissolve

adults and children 12 years and over • take 2 pills every 4 to 6 hours

• do not take more than 8 pills in 24 hours

children ages 6 to under 12 years • take 1 pill every 4 to 6 hours

• do not take more than 4 pills in 24 hours

children ages under 6 years do not use this product in children

under 6 years of age

INACTIVE INGREDIENT

Inactive Ingredients croscarmellose sodium, guar gum, hydroxypropyl cellulose, lecithin,

microcrystalline cellulose, polyethylene glycol, sorbitan monooleate, vegetable oil, xanthan gum